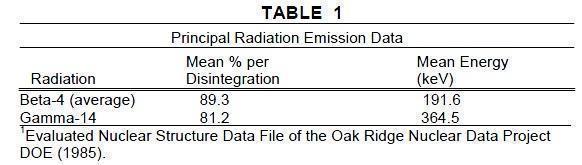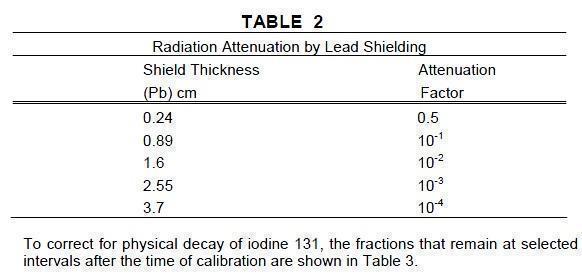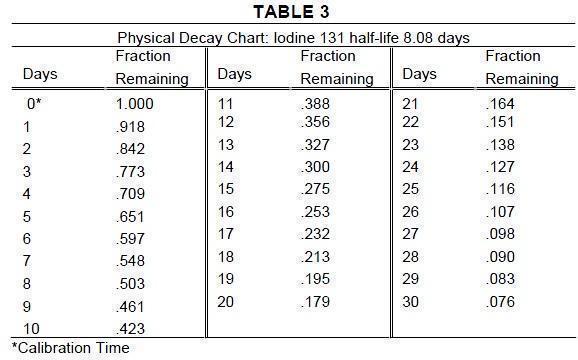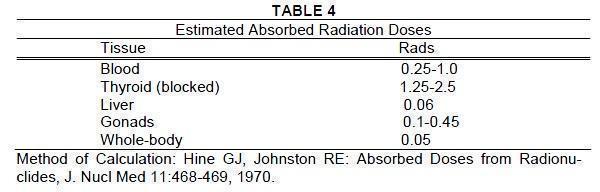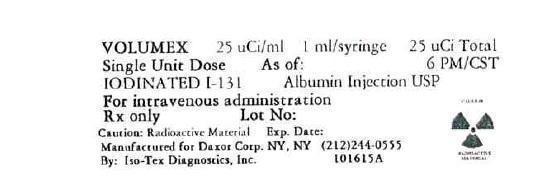 DRUG LABEL: Volumex
NDC: 50914-7720 | Form: INJECTION, SOLUTION
Manufacturer: Iso-Tex Diagnostics, Inc.
Category: prescription | Type: HUMAN PRESCRIPTION DRUG LABEL
Date: 20221121

ACTIVE INGREDIENTS: HUMAN SERUM ALBUMIN I-131 0.025 mCi/1 mL
INACTIVE INGREDIENTS: ALBUMIN HUMAN; BENZYL ALCOHOL

Volumex

Rx Only

DESCRIPTION

Volumex (Iodinated I 131 Albumin Injection) is a diagnostic radiopharmaceutical containing iodinated I 131 albumin for intravenous use. Each mL of sterile, nonpyrogenic, aqueous, colorless to very pale yellow solution provides approximately 10 mg protein (albumin human), 16 mg dibasic sodium phosphate, 1.6 mg monobasic sodium phosphate, not more, than 0.4 mg guanidine hydrochloride, sodium chloride for isotonicity, and 9 mg benzyl alcohol as a preservative. The stabilizer acetyltryptophanate and sodium caprylate have a concentration of less than 0.0089M. The pH has been adjusted to 7.2-7.8 with sodium hydroxide or hydrochloric acid.

Volumex was prepared from blood that was nonreactive when tested for hepatitis B surface antigen (HBsAg). The structure of the complex is unknown.

PHYSICAL CHARACTERISTICS

Iodine 131 decays by beta and gamma emissions with a physical half-life of 8.08 days.^1

Photons that are useful for detection and imaging studies are listed in Table 1.

EXTERNAL RADIATION

The specific gamma ray constant for iodine 131 is 2.2R/hour-millicurie at 1 cm. The first half-value layer is 0.24 cm lead (Pb). A range of values for the relative attenuation of the radiation emitted by this radionuclide that result from interposition of various thicknesses of Pb is shown in Table 2. To facilitate control of the radiation exposure from this radionuclide, the use of a 2.55 cm thickness of Pb will attenuate the radiation emitted by a factor of about 1,000.

CLINICAL PHARMACOLOGY

Following intravenous injection, radioiodinated albumin human is uniformly distributed throughout the intravascular pool within 10 minutes; extravascular distribution takes place more slowly. Iodinated I 131 albumin also can be detected in the lymph and in certain body tissues within 10 minutes after injection, but maximum distribution of radioactivity throughout the extravascular space does not occur until two to four days after administration. The time at which extravascular activity is maximal has been designated as the “equilibrium time.” When this point has been reached, the radioactivity remaining in the intravascular and extravascular spaces decreases slowly and exponentially in parallel fashion.

The administered radioactivity is eliminated almost entirely in the urine, only about 2 percent of the total dose ultimately appearing in the feces.

The biologic half-life of iodinated I 131 albumin is dependent upon a number of factors, and published studies have varied considerably in their reporting of this figure. It has ranged, in the literature, from below 10 days to over 20 days. One important factor affecting the biologic half-life is the initial rate of excretion, and this depends in part on the quality of the iodinated I 131 albumin. With Volumex, the biologic half-life in normal individuals has been reported to be approximately 14 days.

INDICATIONS AND USAGE

Volumex (Iodinated I 131 Allbumin injection) is indicated for use in determinations of total blood and plasma volumes and in protein turnover studies

CONTRAINDICATIONS

None known.

WARNINGS

A few instances of hyperpyrexia and aseptic (chemical) meningeal irritation have been reported

with the use of iodinated I 131 albumin in cisternography. Iodinated I 131 Albumin Injection is not approved for use in cisternography.

PRECAUTIONS

General

In the use of any radioactive material, care should be taken to insure minimum radiation exposure to the patient and occupational workers consistent with proper patient management.

Radiopharmaceuticals should be used only by physicians who are qualified by training and experience in the safe use and handling of radionuclides and whose experience and training have been approved by the appropriate government agency authorized to license the use of radionuclides.

Carcinogenesis, Mutagenesis, Impairment of Fertility

No long-term animal studies have been performed to evaluate carcinogenic potential or whether iodinated I 131 albumin affects fertility in males or females.

Pregnancy Category C

Animal reproduction studies have not been conducted with Iodinated I 131 Albumin Injection. It is also not known whether this agent can cause fetal harm when administered to a pregnant woman or can affect reproduction capacity.

Iodinated I 131 Albumin Injection should be administered to a pregnant woman only if clearly needed.

Ideally, examinations using radiopharmaceuticals, especially those elective in nature, of a woman of childbearing capability should be performed during the first few (approximately 10) days following the onset of menses.

Nursing Mothers

Since iodine 131 is excreted in human milk during lactation, formula feedings should be substituted for breast feedings.

Pediatric use

Safety and effectiveness in children have not been established.

ADVERSE REACTIONS

Although the immunological properties of albumin human are believed to be virtually unaltered by the iodination process, there is a theoretical possibility that allergic reactions may occur in patients receiving additional doses a number of weeks after an initial dose.

DOSAGE AND ADMINISTRATION

Volumex (Iodinated I 131 Albumin Injection) is administered intravenously.

Parenteral drug products should be inspected visually for particulate matter and abnormal coloration prior to administration whenever solution and container permit.

Volumex (Iodinated I 131 Albumin Injection) may be colorless to very pale yellow. Solutions with excessive coloration should not be used.

When a procedure such as a blood volume or a circulation time determination is to be repeated, the total dosage administered in any one week should not exceed 200 microcuries.

To minimize the uptake of radioactive iodine by the thyroid, prior administration of Lugol’s Solution (Strong Iodine Solution USP) may be used. Ten drops of Lugol’s Solution three times daily, beginning at least 24 hours before administration of Volumex and continuing for one or two weeks thereafter, is a suitable dose. Complete assay data for each single unit dose are provided on the container.

Note: The expiration date given on the container pertains to the biologic properties of the material and not to the radioactivity level. It is important to make certain that the radioactivity in the dose at the time of administration is sufficient for the intended use.

The patient dose should be measured by a suitable radioactivity calibration system immediately prior to administration.

Note: A shielded syringe may be used for withdrawing and injecting the iodinated I 131 albumin.

Total Blood and Plasma Volumes

Dosage may range from 5 to 50 microcuries.

Blood Volume Determination

A. Reference Solution

Reference solution is provided with each single unit dose of Volumex. Determine the radioactivity concentration (net cpm/mL) of the reference solution. Care must be taken to assure that the reference solution and the blood samples (Step B3) are assayed using the same geometric configuration.

B. Administration of Dose

1. After withdrawing a background blood sample as described below, insert an intravenous (IV) line into a large vein in patient’s arm. Inject the entire Volumex dose (one milliliter) through the IV line for immediate delivery.Measure the residual radioactivity in the syringe and needle.
2. Destroy syringe after injecting. Do not attempt to resterilize. CAUTION: The syringe should be disposed of in accordance with the US Nuclear Regulatory Commission or Agreement State regulations pertaining to the disposal of radioactive waste.
3. At 12, 18, 24, 30 and 36 minutes after injecting the dose, withdraw blood samples from the patient with a sterile syringe or evacuated sample tube containing anti-coagulant.

C. Calculation of Blood Volume

1. Take a known aliquot from each blood sample and determine radioconcentration in net cpm/mL.

2. Plot the 12, 18, 24, 30 and 36 minute sample counts (net cpm/mL) on semilog graph paper using the average count value of each sample and determine the radioconcentration at injection time (zero time) by drawing a straight line through the 12, 18, 24, 30 and 36 minute points to zero time. The x ordinate of the

graph is the sample withdrawal time and the logarithmic y ordinate is

radioconcentration in net cpm/mL.

3. Calculate patient’s blood volume (in mL) using the following formula:

Net cpm/mL reference solution blood
Net cpm/mL patient’s blood sample x DF = volume
(in mL)

Sample Blood Volume Calculations

Volume of Blood sample aliquot = 1.0 mL

Volume of Reference Solution aliquot = 1.0 mL

Net counts at zero time = 48,100

Net counts obtained from reference solution aliquot = 52, 430

If, for example, DF, dilution factor of the reference solution = 4000

Using the above formula gives = 52,430 x 4000 = 4360 mL

48,100

Serial Blood Volume Determinations

Iodinated I 131 Albumin Injection is administered in sufficiently low dosage to permit repetitions as often as required by clinical circumstances. It must be remembered that it is always necessary to correct for background radioactivity remaining in the blood from former determinations. Therefore, for each determination after the first one, a background blood sample must be taken just before the iodinated I 131 albumin is injected.

Background Blood Sample

1. Withdraw background blood sample from large vein in patient’s sampling arm with a sterile syringe or evacuated sampling tube containing anti-coagulant.
2. Leaving needle in patient’s vein, detach syringe containing blood sample.
3. Attached syringe containing the dose of Volumex to the indwelling IV line and administer (see instructions under Blood Volume Determination, Administration of Dose).
4. Determine radioconcentration in net cpm/mL of aliquots taken from background and postinjection blood samples, and from the reference solution.
5. The radioconcentration (net cpm/mL) per aliquot of the background bloodsample must be subtracted from the radioconcentration per aliquot of the blood sample obtained after the injection of iodinated I 131 albumin. The formula for calculating each blood volume determination after the first one thus becomes:

Net cpm/mL reference solution blood x DF = blood

Net cpm/mL Net cpm/mL volume

postinjection minus background (in mL)

blood sample blood sample

Plasma Volume Determination

The procedure is essentially the same as that for blood volume determination, except that the blood sample drawn from the patient is centrifuged, the red blood cells are removed, and net cpm/mL of the plasma is determined. The formula for calculation of plasma volume, therefore is:

Net cpm/mL reference solution x DF = plasma

Net cpm/mL patient’s plasma sample volume

(in mL)

Protein Turnover Studies

Dosages used have ranged from 10 to 150 microcuries. After injection, a period of seven days should be allowed before determinations are made to permit the elimination of any degraded protein in the dose.

Radiation Dosimetry

The estimated absorbed radiation doses to an average patient (70 kg) from an intravenous injection of 50 microcuries of Iodinated I 131 Albumin Injection USP are shown in Table 4.

For doses of 10, 25, 75, 150, 500 and 750 microcuries, the estimated absorbed

doses are 0.2, 0.5, 1.5, 3, 10 and 15 times the number of rads given, respectively.

HOW SUPPLIED

Volumex (Iodinated I 131 Albumin Injection USP) is available in single unit dose syringes containing 25 microcuries of activity in one milliliter per syringe on the date of calibration. Each single unit dose syringe is supplied with reference solution. Complete assay data for each single unit dose syringe and reference solution are provided on their respective containers. The maximum concentration of a single unit dose syringe of Volumex does not exceed 26.3 microcuries per milliliter at time of calibration

Storage

Store in a refrigerator, 2-8°C (36-46°F)

This radiopharmaceutical is licensed by the Texas Department of Health, Bureau of Radiation Control for distribution to persons licensed

pursuant to 41.26 (b) and Appendix 41-C, Group I and Group II, "Texas Regulations for Control of Radiation," or under equivalent licenses of the

U.S. Nuclear Regulatory Commission, an Agreement State, or a Licensing State.

Manufactured for Daxor Corporation
350 Fifth Avenue, Suite 7120 · New York, NY 10118 · 212-244-0804
by Iso-Tex Diagnostics, Inc., Friendswood, Texas 77546